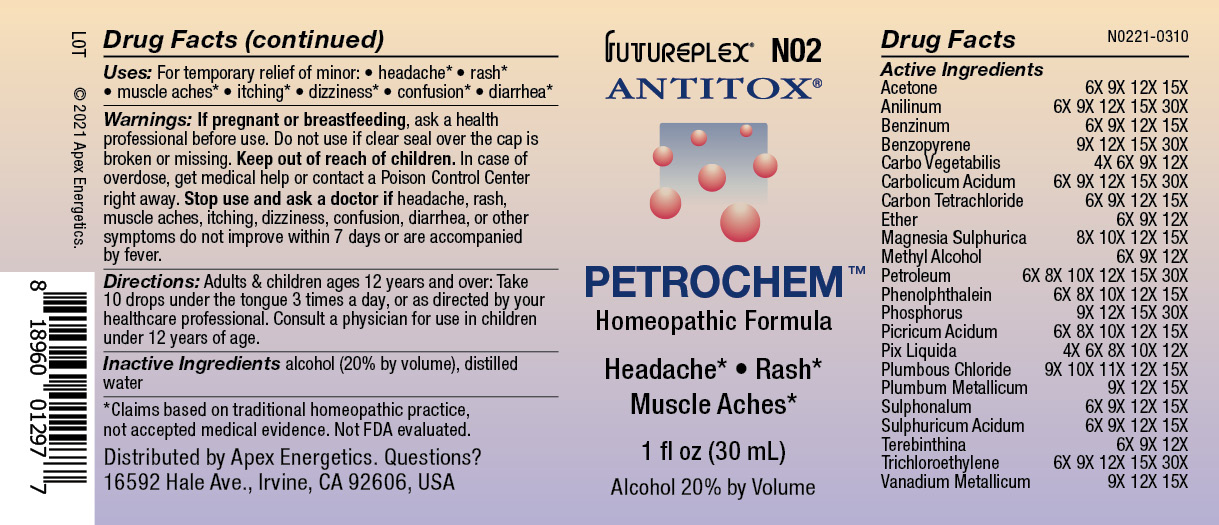 DRUG LABEL: N02
NDC: 63479-1402 | Form: SOLUTION/ DROPS
Manufacturer: Apex Energetics Inc.
Category: homeopathic | Type: HUMAN OTC DRUG LABEL
Date: 20240108
DEA Schedule: CIII

ACTIVE INGREDIENTS: SULFURIC ACID 15 [hp_X]/1 mL; ACETONE 15 [hp_X]/1 mL; PICRIC ACID 15 [hp_X]/1 mL; PINE TAR 12 [hp_X]/1 mL; SULFONMETHANE 15 [hp_X]/1 mL; VANADIUM 15 [hp_X]/1 mL; ACTIVATED CHARCOAL 12 [hp_X]/1 mL; ANILINE 30 [hp_X]/1 mL; BENZENE 15 [hp_X]/1 mL; PHENOL 30 [hp_X]/1 mL; METHYL ALCOHOL 12 [hp_X]/1 mL; KEROSENE 30 [hp_X]/1 mL; PHENOLPHTHALEIN 15 [hp_X]/1 mL; TURPENTINE OIL 12 [hp_X]/1 mL; BENZO(A)PYRENE 30 [hp_X]/1 mL; CARBON TETRACHLORIDE 15 [hp_X]/1 mL; TRICHLOROETHYLENE 30 [hp_X]/1 mL; ETHER 12 [hp_X]/1 mL; MAGNESIUM SULFATE HEPTAHYDRATE 15 [hp_X]/1 mL; PHOSPHORUS 30 [hp_X]/1 mL; LEAD CHLORIDE 15 [hp_X]/1 mL; LEAD 15 [hp_X]/1 mL
INACTIVE INGREDIENTS: WATER; ALCOHOL

N02

Active Ingredients
Acetone | 6X 9X 12X 15X
Anilinum | 6X 9X 12X 15X 30X
Benzinum | 6X 9X 12X 15X
Benzopyrene | 9X 12X 15X 30X
Carbo Vegetabilis | 4X 6X 9X 12X
Carbolicum Acidum | 6X 9X 12X 15X 30X
Carbon Tetrachloride | 6X 9X 12X 15X
Ether | 6X 9X 12X
Magnesia Sulphurica | 8X 10X 12X 15X
Methyl Alcohol | 6X 9X 12X
Petroleum | 6X 8X 10X 12X 15X 30X
Phenolphthalein | 6X 8X 10X 12X 15X
Phosphorus | 9X 12X 15X 30X
Picricum Acidum | 6X 8X 10X 12X 15X
Pix Liquida | 4X 6X 8X 10X 12X
Plumbous Chloride | 9X 10X 11X 12X 15X
Plumbum Metallicum | 9X 12X 15X
Sulphonalum | 6X 9X 12X 15X
Sulphuricum Acidum | 6X 9X 12X 15X
Terebinthina | 6X 9X 12X
Trichloroethylene | 6X 9X 12X 15X 30X
Vanadium Metallicum | 9X 12X 15X

Uses:

PURPOSE

Uses: For temporary relief of minor:

headache*

rash*

muscle aches*

itching*

dizziness*

confusion*

diarrhea*

*Claims based on traditional homeopathic practice, not accepted medical evidence. Not FDA evaluated.

Warnings:

PREGNANCY OR BREAST FEEDING

If pregnant or breastfeeding, ask a health professional before use.

Do not use if clear seal over the cap is broken or missing.

Keep out of reach of children. In case of overdose, get medical help or contact a Poison Control Center right away.

Stop use and ask a doctor if headache, rash, muscle aches, itching, dizziness, confusion, diarrhea, or other symptoms do not improve within 7 days or are accompanied by fever.

DOSAGE AND ADMINISTRATION

Directions: Adults & children ages 12 years and over: Take 10 drops under the tongue 3 times a day, or as directed by your healthcare professional. Consult a physician for use in children under 12 years of age.

INACTIVE INGREDIENT

alcohol (20% by volume), distilled water

Distributed by Apex Energetics. Questions?

16592 Hale Ave., Irvine, CA 92606, USA

PACKAGE LABEL

FUTUREPLEX® N02

ANTITOX®

PETROCHEM™

Homeopathic Formula

Headache*

Rash*

Muscle Aches*

1 fl oz (30 mL)

Alcohol 20% by Volume